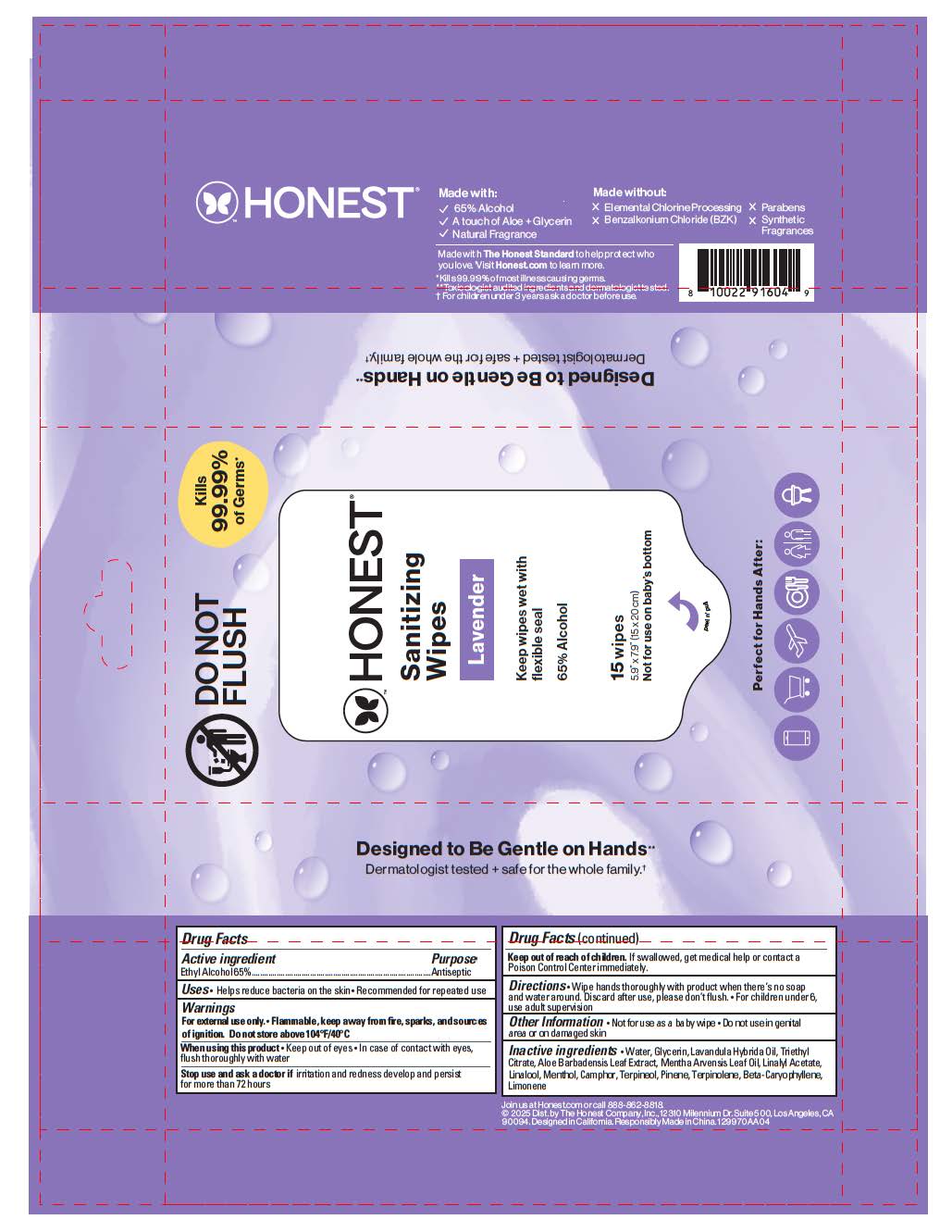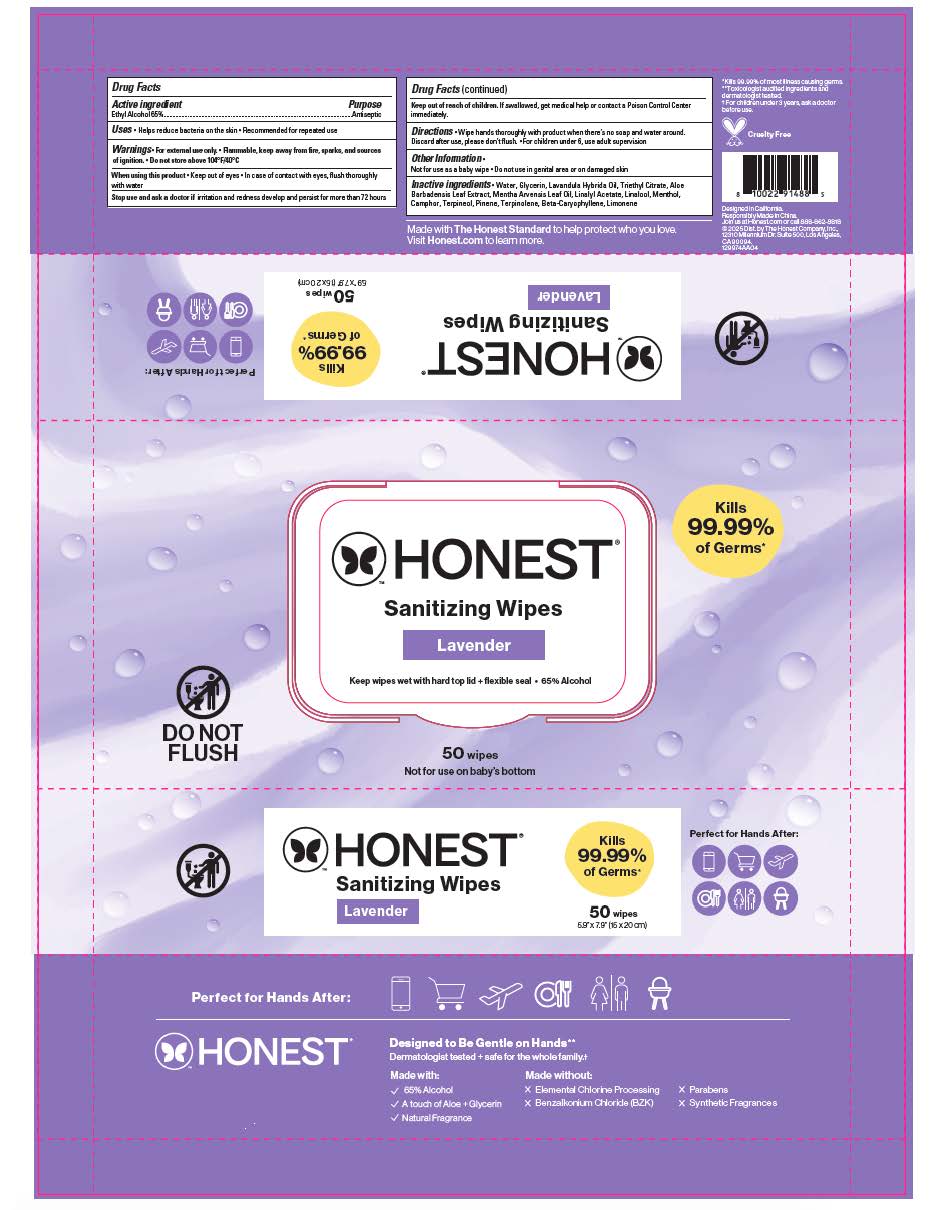 DRUG LABEL: Sanitizing Wipes Lavender
NDC: 69366-319 | Form: CLOTH
Manufacturer: The Honest Company Inc.
Category: otc | Type: HUMAN OTC DRUG LABEL
Date: 20260209

ACTIVE INGREDIENTS: ALCOHOL 65 mL/100 mL
INACTIVE INGREDIENTS: CAMPHOR (NATURAL); TERPINOLENE; LIMONENE, (+)-; TERPINEOL; PINENE; GLYCERIN; ALOE BARBADENSIS LEAF; BETA-CARYOPHYLLENE; TRIETHYL CITRATE; LINALYL ACETATE; MENTHOL; LAVANDULA HYBRIDA OIL; MENTHA ARVENSIS LEAF OIL; WATER; LINALOOL

ACTIVE INGREDIENT

Ethyl Alcohol 65%

PURPOSE

Antiseptic

OTHER SAFETY INFORMATION

- Not for use as a baby wipe
- Do not use in genital area or on damaged skin

INDICATIONS AND USAGE

- Helps reduce bacteria on the skin
- Recommended for repeated use

WARNINGS

For external use only. Flammable, keep away from fire, sparks, and sources or ignition. Do not store above 104°F/40°C

WHEN USING

- Keep out of eyes
- In case of contact with eyes, flush thoroughly with water

Stop use and ask a doctor if irritation and redness develop and persist for more than 72 hours

KEEP OUT OF REACH OF CHILDREN

If swallowed, get medical help or contact a Poison Control Center immediately.

INACTIVE INGREDIENT

Water, Glycerin, Lavandula Hybrida Oil, Triethyl Citrate, Aloe Barbadensis Leaf Extract, Mentha Arvensis Leaf Oil, Linalyl Acetate, Linalool, Menthol, Camphor, Terpineol, Pinene, Terpinolene, Beta-Caryophyllene, Limonene

DOSAGE AND ADMINISTRATION

- Wipe hands thoroughly with product when there's no soap and water around. Discard after use, please don't flush.
- For children under 6, use adult supervision